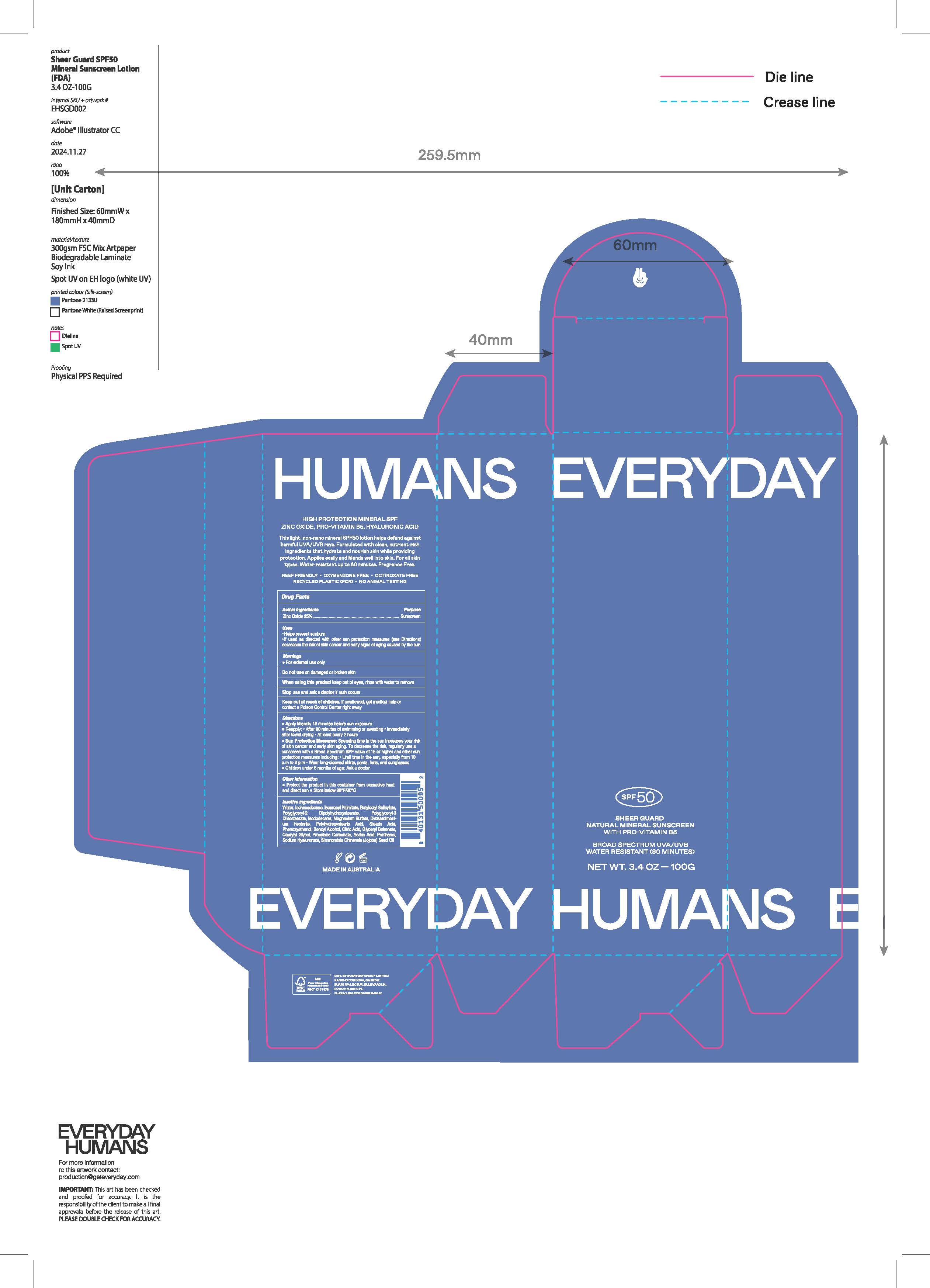 DRUG LABEL: Sheer Guard Natural Mineral Sunscreen
NDC: 72098-020 | Form: CREAM
Manufacturer: EVERYDAY GROUP LIMITED
Category: otc | Type: HUMAN OTC DRUG LABEL
Date: 20251204

ACTIVE INGREDIENTS: ZINC OXIDE 25 mg/1 mL
INACTIVE INGREDIENTS: PROPYLENE CARBONATE; SODIUM HYALURONATE; POLYGLYCERYL-3 DIISOSTEARATE; BUTYLOCTYL SALICYLATE; ISOPROPYL PALMITATE; POLYGLYCERYL-2 DIPOLYHYDROXYSTEARATE; ISODODECANE; MAGNESIUM SULFATE; DISTEARDIMONIUM HECTORITE; POLYHYDROXYSTEARIC ACID (2300 MW); STEARIC ACID; PHENOXYETHANOL; BENZYL ALCOHOL; CITRIC ACID; ETHYLHEXYLGLYCERYL BEHENATE; WATER; PANTHENOL; SIMMONDSIA CHINENSIS (JOJOBA) SEED OIL; SORBIC ACID; CAPRYLYL GLYCOL

Sheer Guard Natural Mineral Sunscreen

Active ingredients

Zinc Oxide 25%

Purpose

Sunscreen

Uses

- helps prevent sunburn
- if used as directed with other sun protection measures (see) decreases the risk of skin cancer and early skin aging caused by the sun Directions

Warnings

- For external use only

Do not use

on damaged or broken skin

When using this product

keep out of eyes, rinse with water to remove

Stop use and ask a doctor

if rash occurs

Keep out of reach of children.

If swallowed, get medical help or contact a Poison Control Center right away

Directions

- apply liberally 15 minutes before sun exposure
- reapply: after 80 minutes of swimming or sweating. Immediately after towel drying. At least every 2 hours.
- Sun Protection Measures:
- Spending time in the sun increases your risk of skin cancer and early skin aging. To decrease the risk, regularly use a sunscreen with a Broad Spectrum SPF value of 15 or higher and other sun protection measures including:
- limit time in the sun, especially from 10 a.m. to 2 p.m.
- wear long-sleeved shirts, pants, hats, and sunglasses
- children under 6 months of age: Ask a doctor

Other information

- protect the product in this container from excessive heat and direct sun.
- store below 86°F/30° C

Inactive ingredients

Water, Isohexedecane, Isopropyl Palmitate, Butyloctyl Salicylate, Polyglyceryl-2 Dipolyhydroxystearate, Polyglyceryl-3 Diisostearate, Isododecane, Magnesium Sulfate, Disteardimonium Hectorite, Polyhydroxystearic Acid, Stearic Acid, Phenoxyethanol, Benzyl Alcohol, Citric Acid, Glyceryl Behenate, Caprylyl Glycol, Propylene Carbonate, Sorbic Acid, Panthenol, Sodium Hyaluronate, Simmondsia Chinensis (Jojoba) Seed Oil